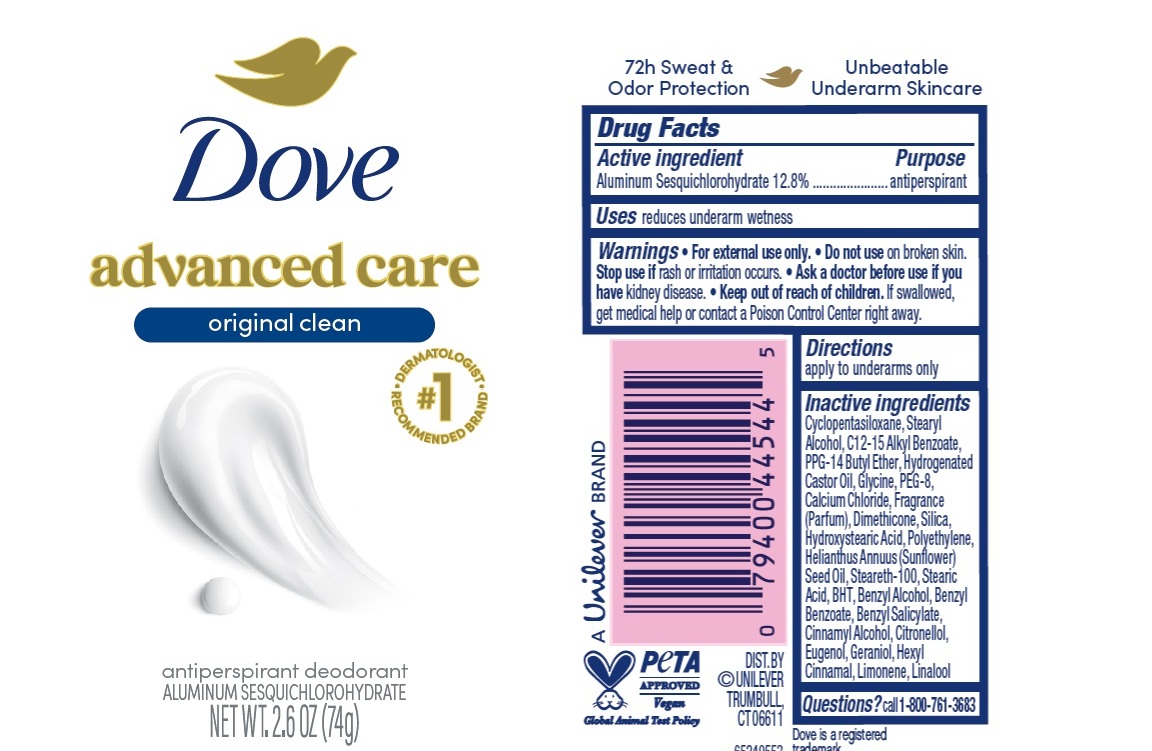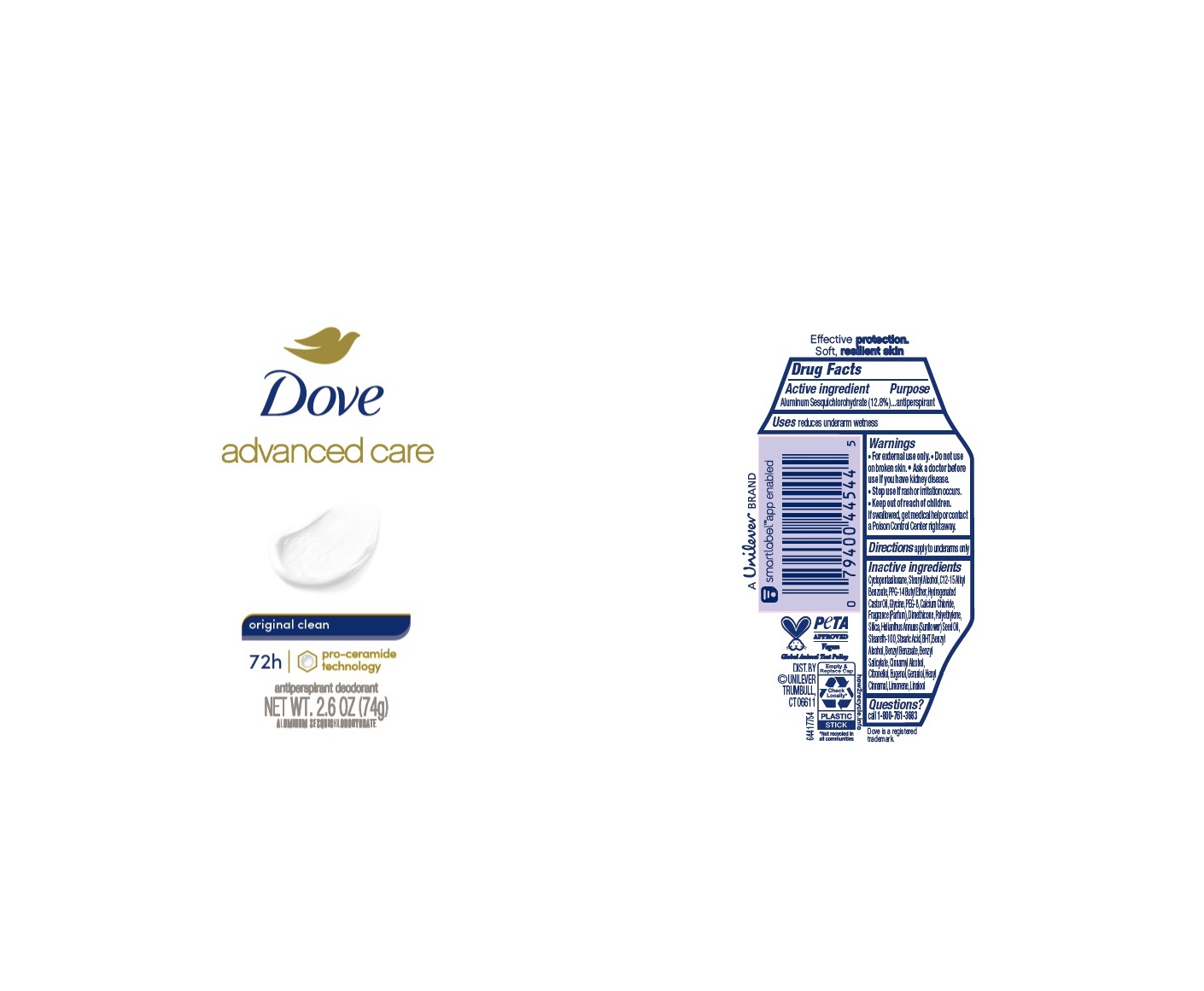 DRUG LABEL: Dove
NDC: 64942-2328 | Form: STICK
Manufacturer: Conopco Inc. d/b/a/ Unilever
Category: otc | Type: HUMAN OTC DRUG LABEL
Date: 20260220

ACTIVE INGREDIENTS: ALUMINUM SESQUICHLOROHYDRATE 12.8 g/100 g
INACTIVE INGREDIENTS: EUGENOL; LIMONENE, (+)-; CYCLOMETHICONE 5; BENZYL SALICYLATE; STEARIC ACID; CALCIUM CHLORIDE; LINALOOL, (+/-)-; HIGH DENSITY POLYETHYLENE; HYDROGENATED CASTOR OIL; BUTYLATED HYDROXYTOLUENE; PPG-14 BUTYL ETHER; STEARYL ALCOHOL; SUNFLOWER OIL; SILICON DIOXIDE; ALKYL (C12-15) BENZOATE; DIMETHICONE; STEARETH-100; POLYETHYLENE GLYCOL 400; BENZYL ALCOHOL; .BETA.-CITRONELLOL, (R)-; GLYCINE; BENZYL BENZOATE; CINNAMYL ALCOHOL; .ALPHA.-HEXYLCINNAMALDEHYDE; GERANIOL

Dove Advanced Care Original Clean 72h Antiperspirant Deodorant

Drug Facts

Active ingredient

Aluminum Sesquichlorohydrate (12.8)

Purpose

antiperspirant

Uses

reduces underarm wetness

Warnings

• For external use only.
• Do not use on broken skin .
• Ask a doctor before use if you have kidney disease.
• Stop use if rash or irritation occurs.

• Keep out of reach of children.

If swallowed, get medical help or contact a Poison Control Center right away.

Directions

apply to underarms only

Inactive ingredients

Cyclopentasiloxane, Stearyl Alcohol, C12-15 Alkyl Benzoate, PPG-14 Butyl Ether, Hydrogenated Castor Oil, Glycine, PEG-8, Calcium Chloride, Fragrance (Parfum), Dimethicone, Polyethylene, Silica, Helianthus Annuus (Sunflower) Seed Oil, Steareth-100, Stearic Acid, BHT, Benzyl Alcohol, Benzyl Benzoate, Benzyl Salicylate, Cinnamyl Alcohol, Citronellol, Eugenol, Geraniol, Hexyl Cinnamal, Limonene, Linalool

Questions?

Call 1-800-761-3683